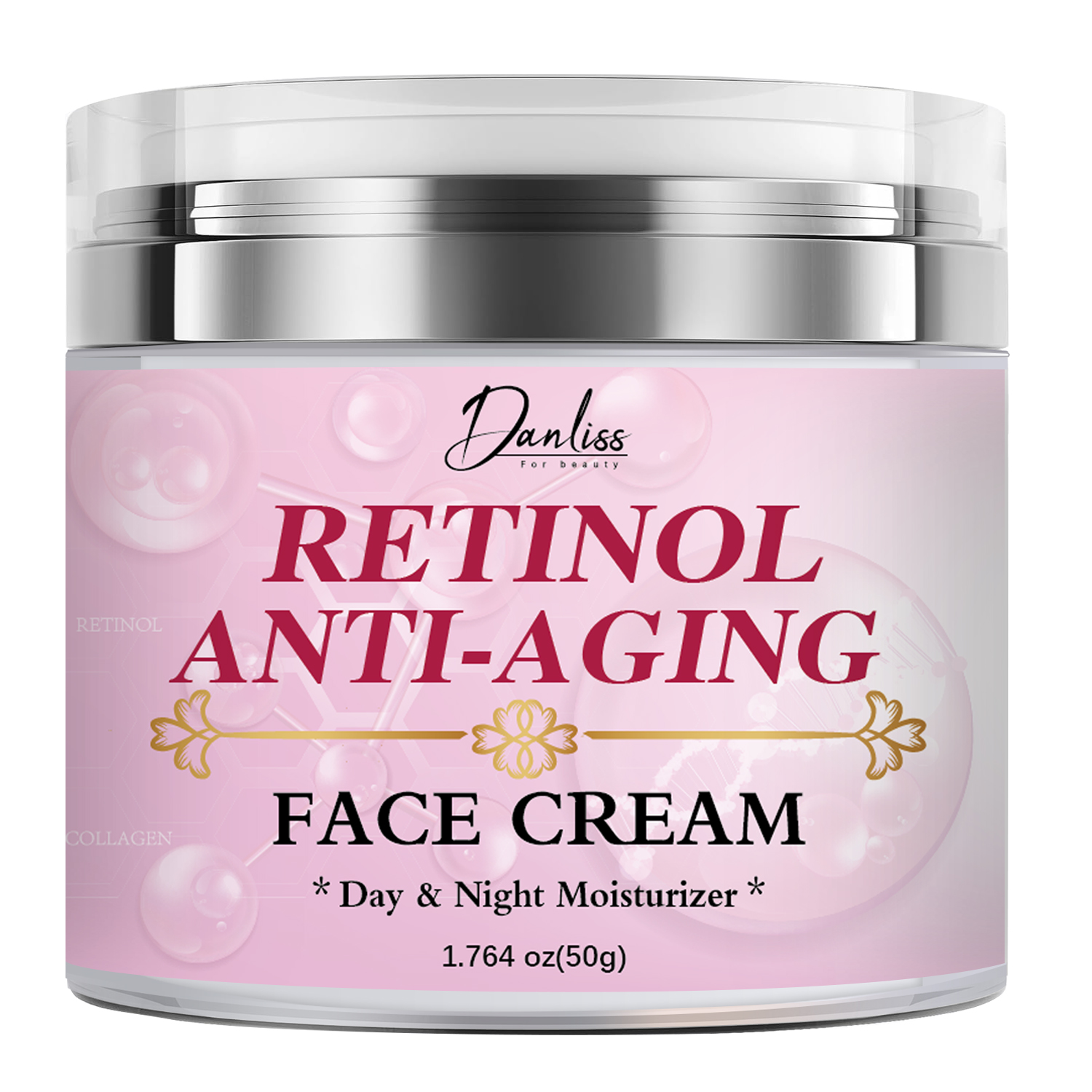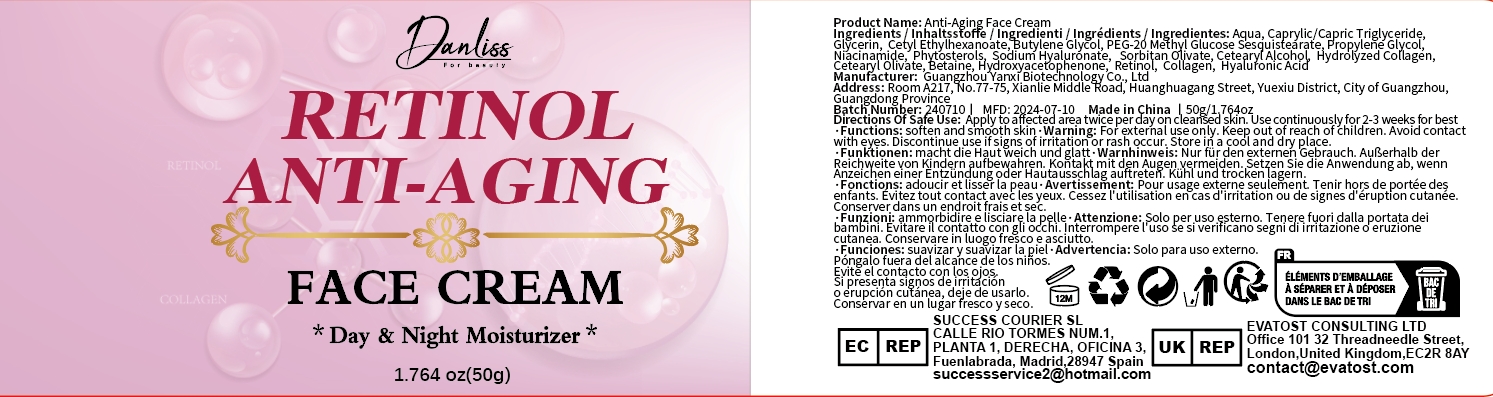 DRUG LABEL: Anti-Aging Face Cream
NDC: 84025-090 | Form: CREAM
Manufacturer: Guangzhou Yanxi Biotechnology Co.. Ltd
Category: otc | Type: HUMAN OTC DRUG LABEL
Date: 20240725

ACTIVE INGREDIENTS: GLYCERIN 5 mg/50 g; CETYL ETHYLHEXANOATE 3 mg/50 g
INACTIVE INGREDIENTS: WATER

DOSAGE AND ADMINISTRATION

For daily skin care

WARNINGS

Keep out of children

INACTIVE INGREDIENT

Aqua

INDICATIONS AND USAGE

For aging skin

Keep out of children

PURPOSE

Slows down skin aging and keeps skin moisturized